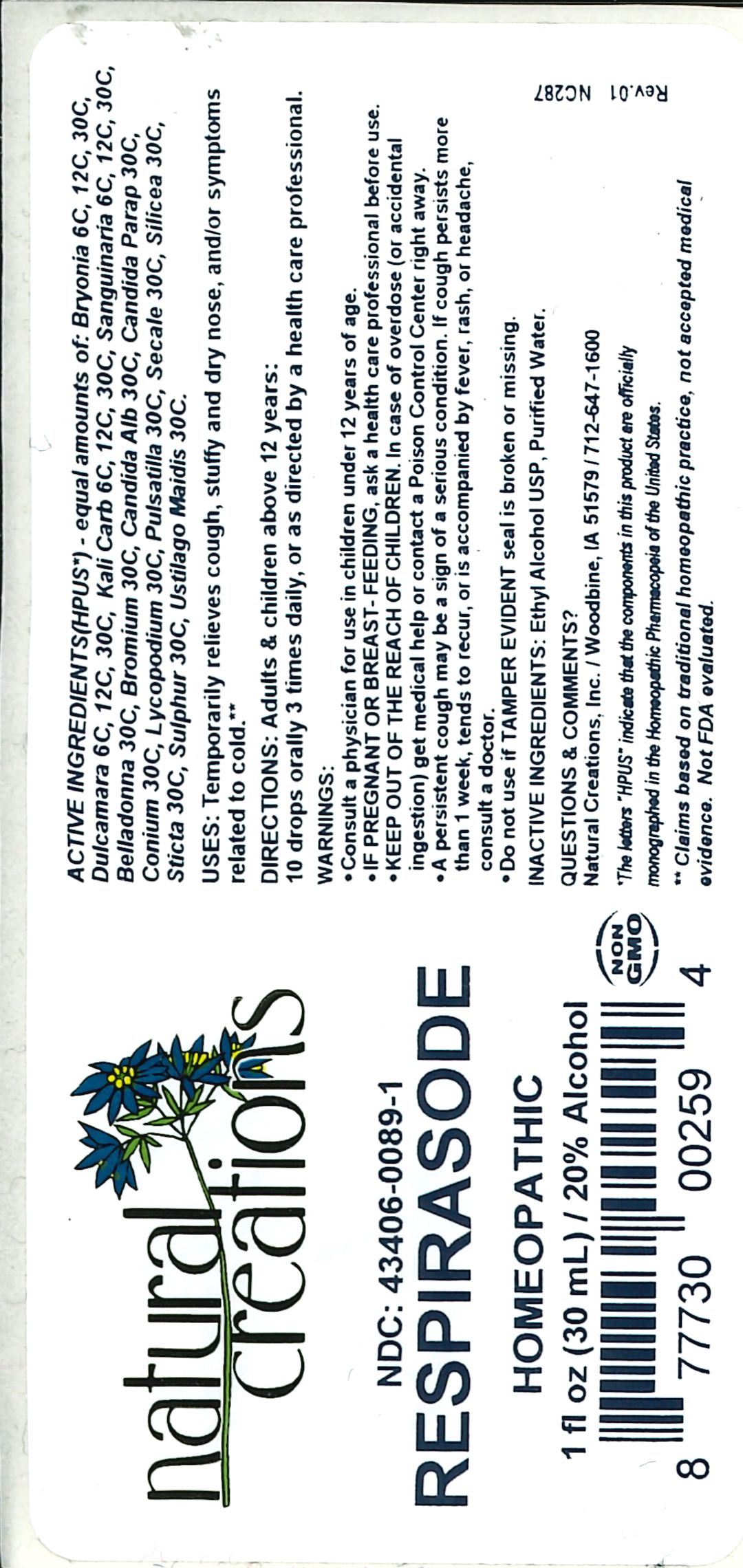 DRUG LABEL: Respirasode
NDC: 43406-0089 | Form: LIQUID
Manufacturer: Natural Creations, Inc
Category: homeopathic | Type: HUMAN OTC DRUG LABEL
Date: 20251216

ACTIVE INGREDIENTS: BRYONIA ALBA ROOT 30 [hp_C]/1 mL; SOLANUM DULCAMARA TOP 30 [hp_C]/1 mL; POTASSIUM CARBONATE 30 [hp_C]/1 mL; SANGUINARIA CANADENSIS ROOT 30 [hp_C]/1 mL; ATROPA BELLADONNA 30 [hp_C]/1 mL; BROMINE 30 [hp_C]/1 mL; CANDIDA ALBICANS 30 [hp_C]/1 mL; CANDIDA PARAPSILOSIS 30 [hp_C]/1 mL; CONIUM MACULATUM FLOWERING TOP 30 [hp_C]/1 mL; LYCOPODIUM CLAVATUM SPORE 30 [hp_C]/1 mL; PULSATILLA VULGARIS WHOLE 30 [hp_C]/1 mL; CLAVICEPS PURPUREA SCLEROTIUM 30 [hp_C]/1 mL; SILICON DIOXIDE 30 [hp_C]/1 mL; LOBARIA PULMONARIA 30 [hp_C]/1 mL; SULFUR 30 [hp_C]/1 mL; USTILAGO MAYDIS 30 [hp_C]/1 mL
INACTIVE INGREDIENTS: ALCOHOL; WATER

Respirasode

ACTIVE INGREDIENT

ACTIVE INGREDIENTS (HPUS*) - equal amounts of: Bryonia 6C, 12C, 30C, Dulcamara 6C, 12C, 30C, Kali Carb 6C, 12C, 30C, Sanguinaria 6C, 12C, 30C, Belladonna 30C, Bromium 30C, Candida Alb 30C, Candida Parap 30C, Conium 30C, Lycopodium 30C, Pulsatilla 30C, Secale 30C, Silicea 30C, Sticta 30C, Sulphur 30C, Ustilago Maidis 30C

INDICATIONS AND USAGE

USES: Temporarily relieves cough, stuffy and dry nose, and/or symptoms related to cold.**

PURPOSE

USES: Temporarily relieves cough, stuffy and dry nose, and/or symptoms related to cold.**

DOSAGE AND ADMINISTRATION

DIRECTIONS: Adults & children above 12 years: 10 drops orally 3 times daily, or as directed by a health care professional.

KEEP OUT OF REACH OF CHILDREN

KEEP OUT OF THE REACH OF CHILDREN. In case of overdose (or accidental ingestion) get medical help or contact a Poison Control Center right away.

WARNINGS:

- Consult a physician for use in children under 12 years of age.
- IF PREGNANT OR BREAST-FEEDING, ask a health care professional before use.
- KEEP OUT OF THE REACH OF CHILDREN. In case of overdose (or accidental ingestion) get medical help or contact a Poison Control Center right away.
- A persistent cough may be a sign of a serious condition. If cough persists more than 1 week, tends to recur, or is accompanied by fever, rash, or headache, consult a doctor.
- Do not use if TAMPER EVIDENT seal is broken or missing.

INACTIVE INGREDIENTS: Ethyl Alcohol USP, Purified Water

QUESTIONS & COMMENTS?

Natural Creations, Inc. / Woodbine, IA 51579 / 712-647-1600

REFERENCES

*The letters "HPUS" indicate the components in the product are officially monographed in the Homeopathic Pharmacopeia of the United States.

**Claims based on traditional homeopathic practice, not accepted medical evidence. Not FDA evaluated.

PACKAGE LABEL

NDC:43406-0089-1

Respirasode

HOMEOPATHIC

1 fl oz (30mL) / 20% Alcohol